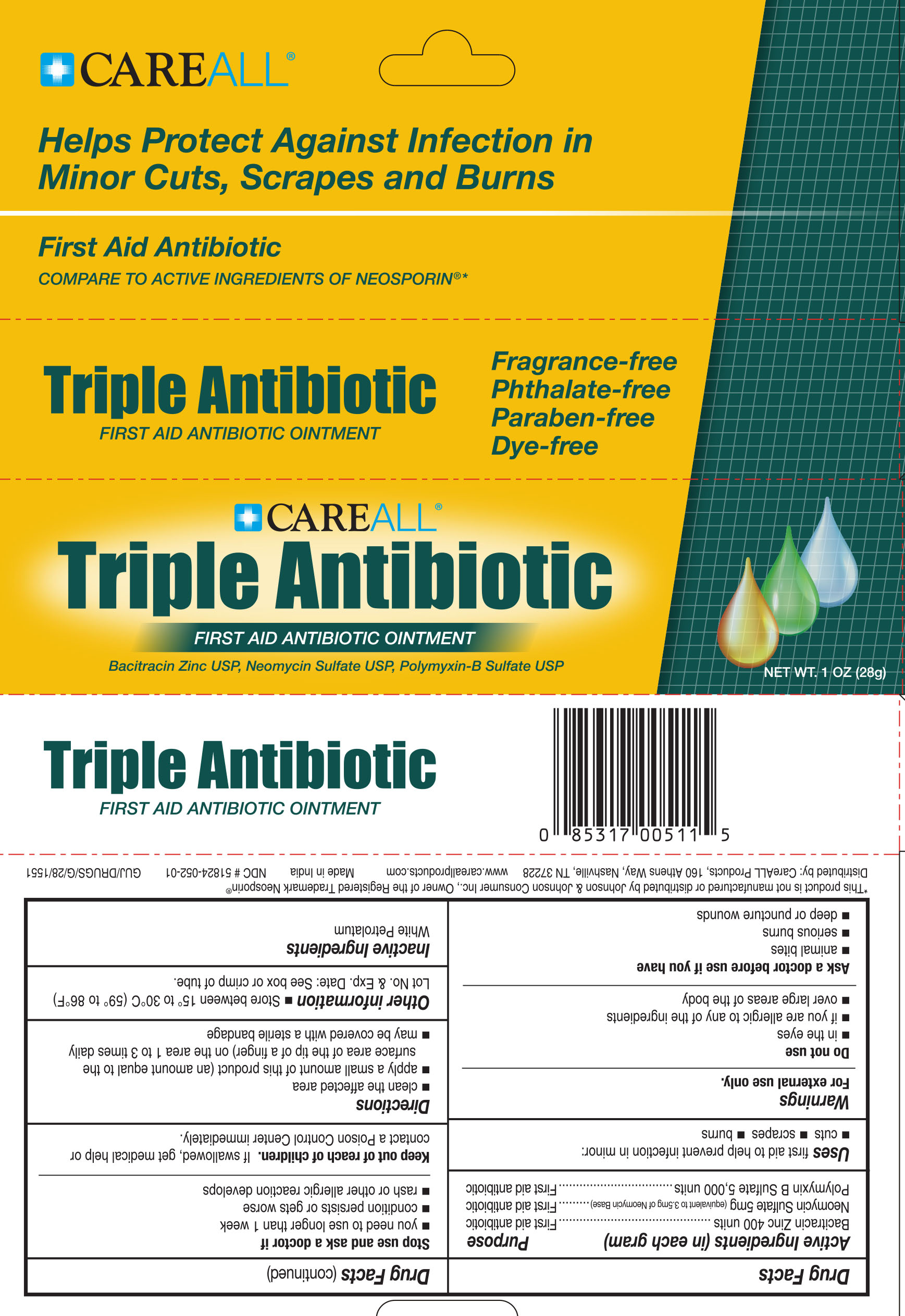 DRUG LABEL: CareALL Triple Antibiotic
NDC: 51824-052 | Form: OINTMENT
Manufacturer: New World Imports, Inc
Category: otc | Type: HUMAN OTC DRUG LABEL
Date: 20251201

ACTIVE INGREDIENTS: BACITRACIN ZINC 400 [USP'U]/1 g; NEOMYCIN SULFATE 5 mg/1 g; POLYMYXIN B SULFATE 5000 [USP'U]/1 g
INACTIVE INGREDIENTS: WHITE PETROLATUM

Active Ingredients (in each gram)

Bacitracin Zinc 400 units

Neomycin Sulfate 5 mg

Polymyxin B Sulfate 5,000 units

PURPOSE

First aid antibiotic

Keep out of reach of children. If swallowed, get medical help or contact a poison control center immediately

INDICATIONS AND USAGE

First aid to help prevent infection in minor cuts, scrapes and burns

WARNINGS

For external use only

Do not use

In the eyes

If you are allergic to any of the ingredients

Over large areas of the body

Ask a doctor before use if you have

Animal bites

Serious Burns

Deep or puncture wounds

Stop use and ask a doctor if

You need to use longer than 1 week

condition persists or gets worse

rash or other allergic reaction develops

DOSAGE AND ADMINISTRATION

Clean the affected area

Apply a small amount of this product (an amount equal to the surface of th tip of a finger) on the area 1 to 3 times daily

May be covered with a sterile bandage

INACTIVE INGREDIENT

White Petrolatum